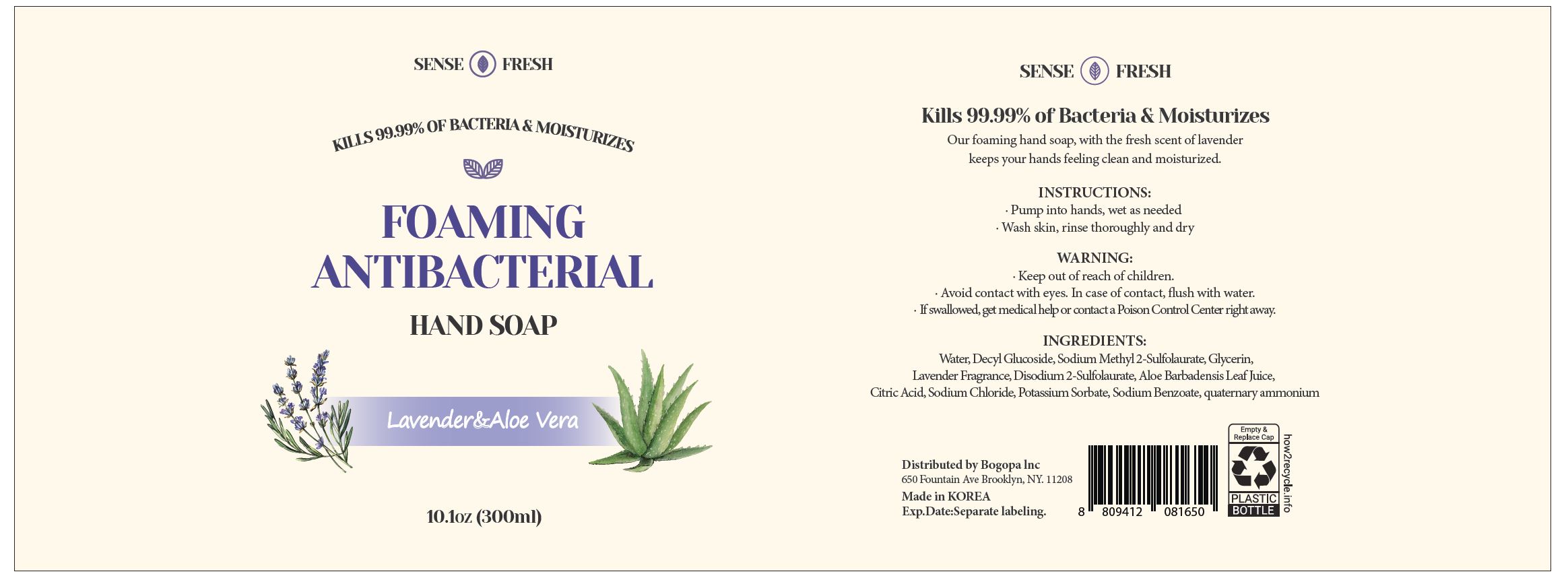 DRUG LABEL: Sense fresh Foaming Anti bacterial handsoap
NDC: 74085-0009 | Form: LIQUID
Manufacturer: BIOCHEM KOREA CO LTD
Category: otc | Type: HUMAN OTC DRUG LABEL
Date: 20201224

ACTIVE INGREDIENTS: BENZALKONIUM CHLORIDE 0.1 g/100 mL
INACTIVE INGREDIENTS: WATER

Drug Facts

ACTIVE INGREDIENT

Benzalkonium chloride

PURPOSE

Our foaming hand soap, with the fresh scent of lavender keeps your hands feeling clean and moisturized.

KEEP OUT OF REACH OF THE CHILDREN

INDICATIONS AND USAGE

· Pump into hands, wet as needed
· Wash skin, rinse thoroughly and dry

WARNINGS

■ For external use only.

■ Do not use in eyes.

■ lf swallowed, get medical help promptly.

■ Stop use, ask doctor lf irritation occurs.

■ Keep out of reach of children.

DOSAGE AND ADMINISTRATION

for external use only

INACTIVE INGREDIENT

Decyl Glucoside

Sodium Methyl 2-Sulfolaurate

Glycerin

Disodium 2-Sulfolaurate

Aloe Barbadensis Leaf Juice

Citric Acid

Sodium Chloride

Potassium Sorbate

Sodium Benzoate

Lavender Fragrance

water